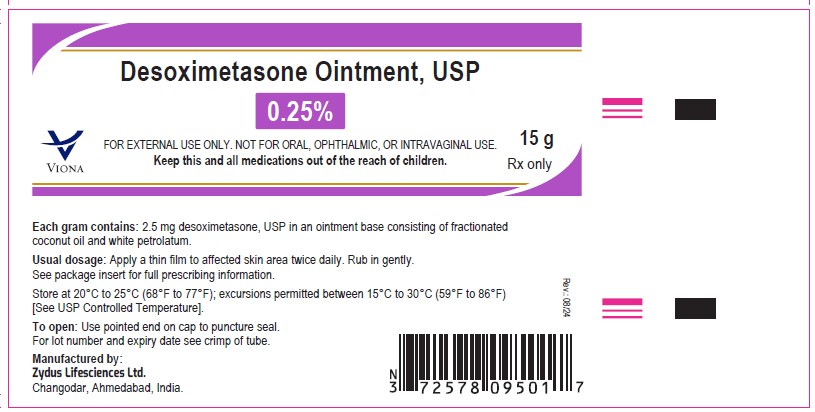 DRUG LABEL: desoximetasone
NDC: 70771-1166 | Form: OINTMENT
Manufacturer: Zydus Lifesciences Limited
Category: prescription | Type: HUMAN PRESCRIPTION DRUG LABEL
Date: 20240814

ACTIVE INGREDIENTS: DESOXIMETASONE 2.5 mg/1 g
INACTIVE INGREDIENTS: COCONUT OIL; PETROLATUM

Desoximetasone Ointment, USP

PACKAGE LABEL.PRINCIPAL DISPLAY PANEL

Desoximetasone Ointment USP, 0.25%

NDC – 70771-1166-1 for 15 gm tube